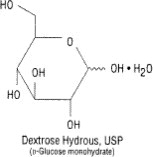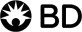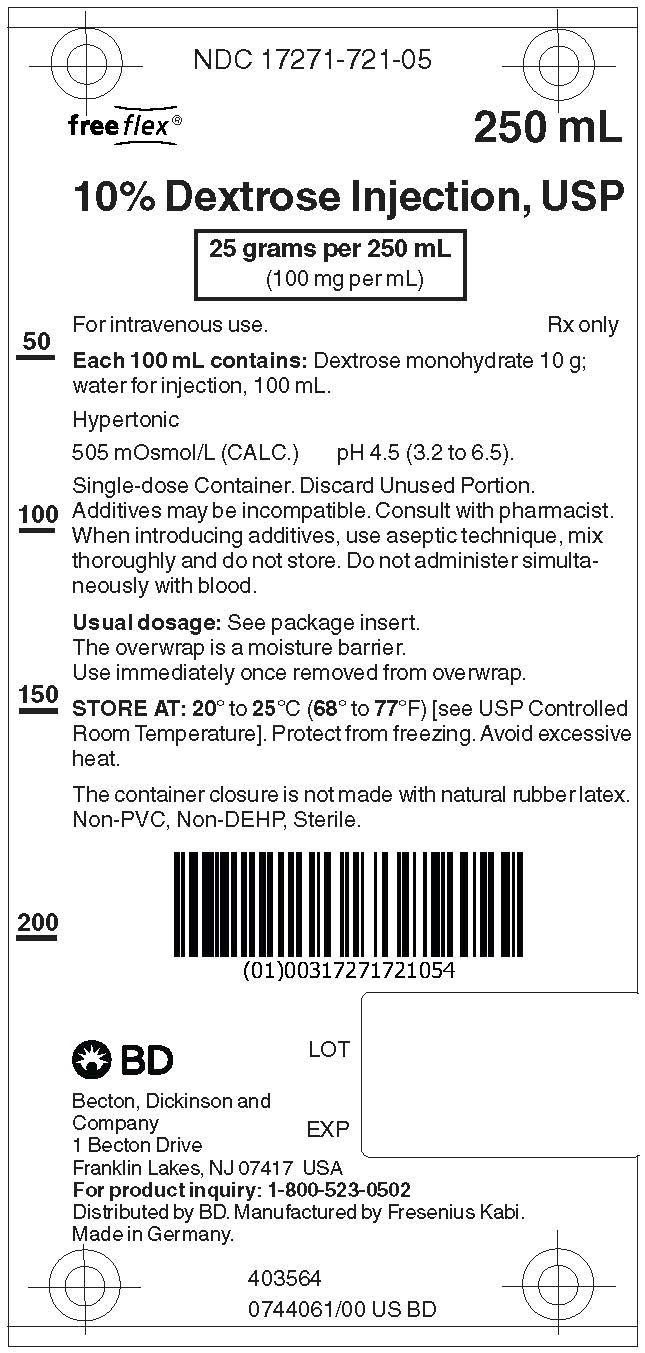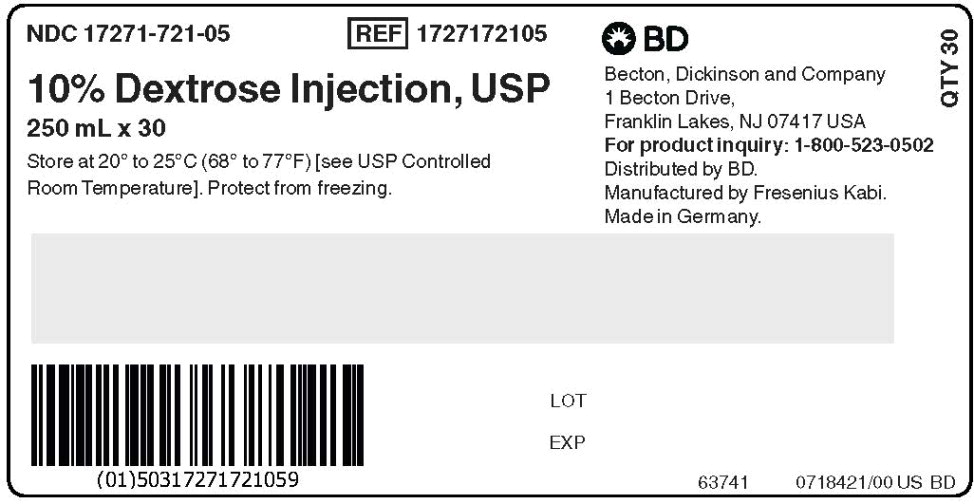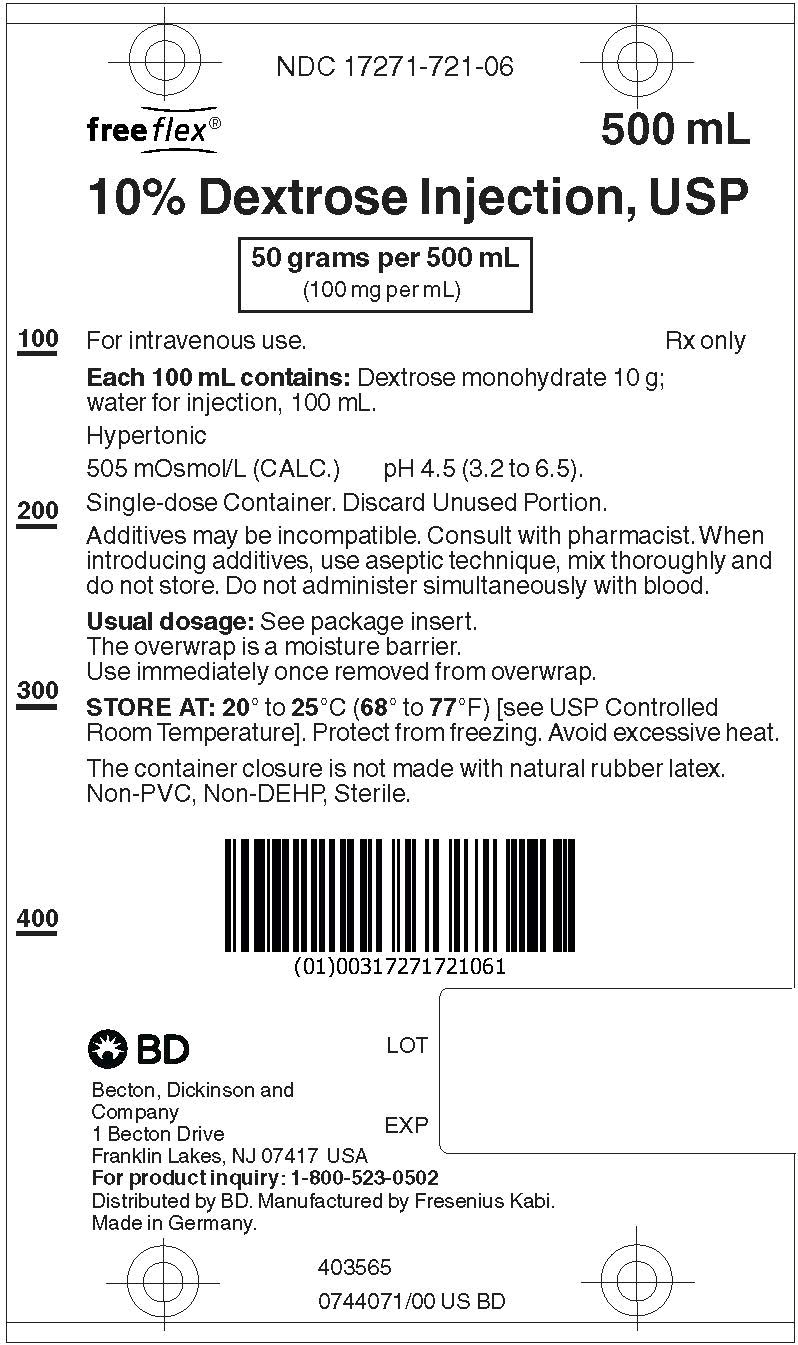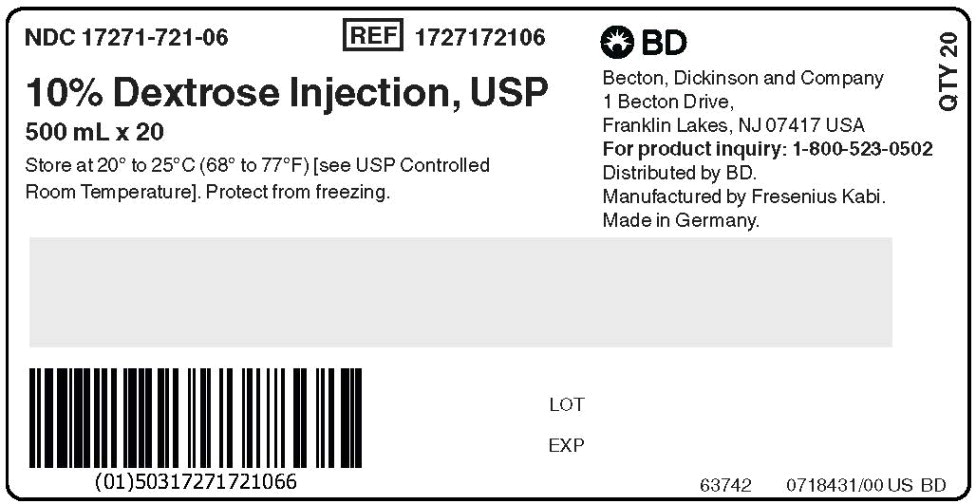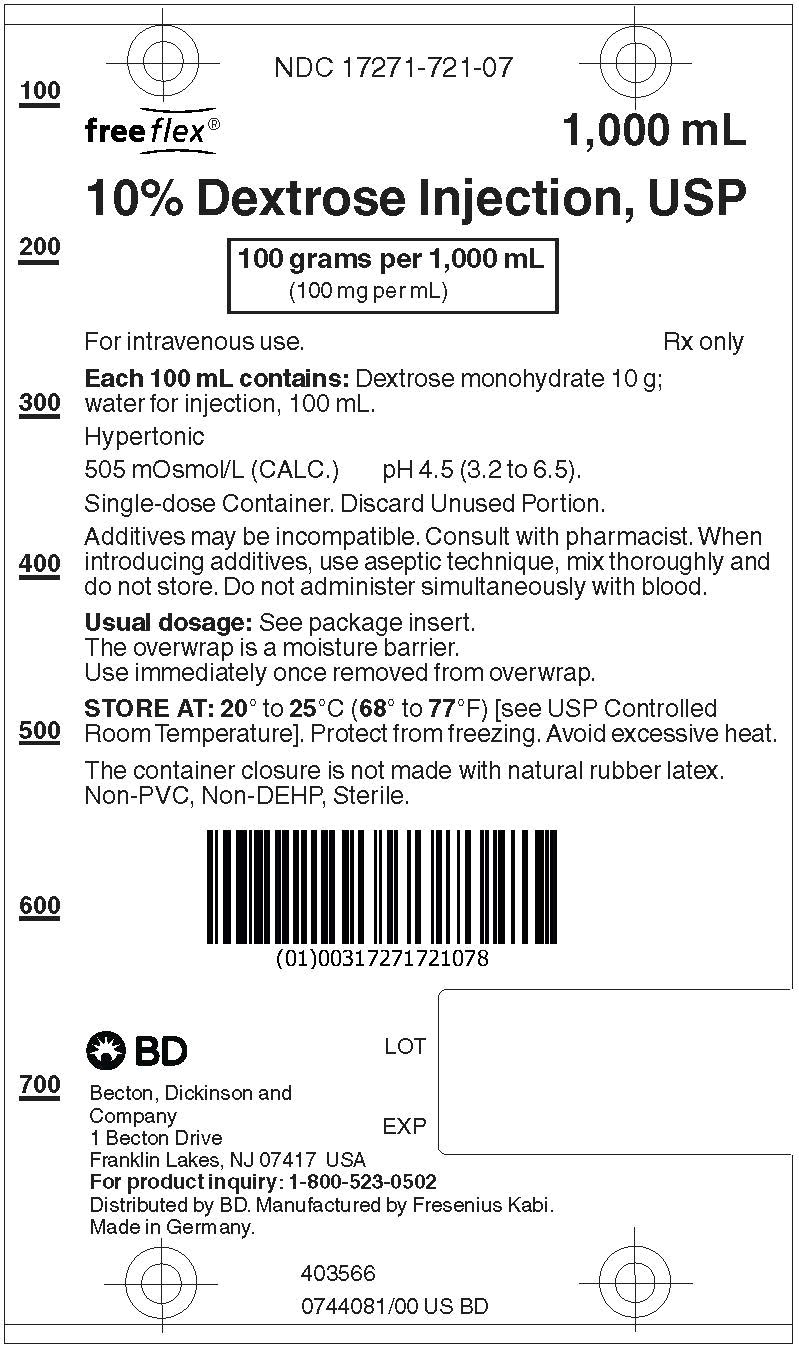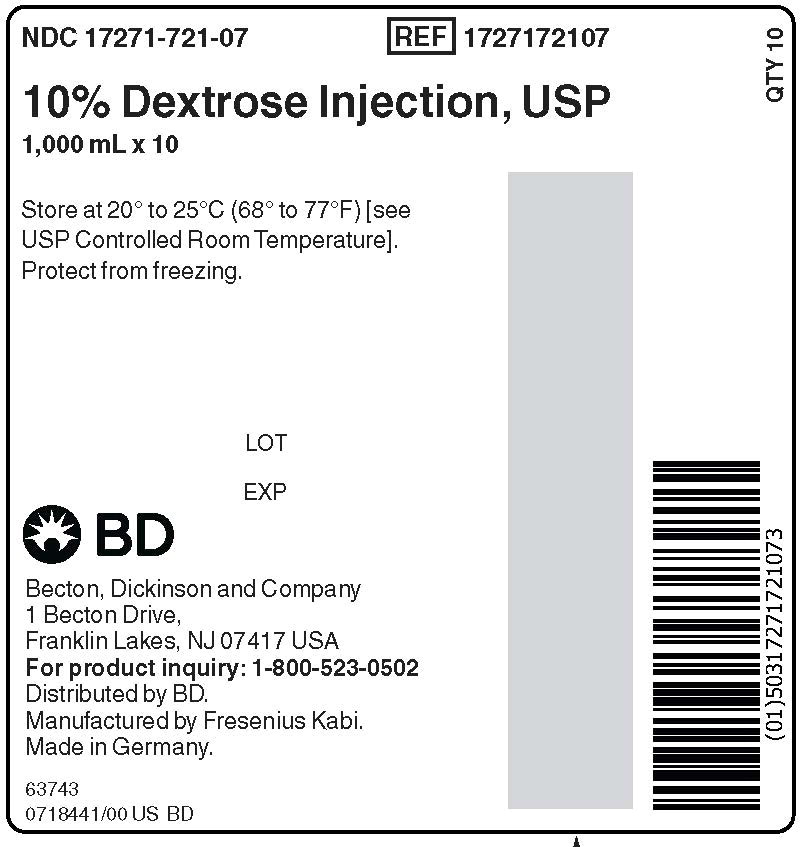 DRUG LABEL: Dextrose
NDC: 17271-721 | Form: INJECTION, SOLUTION
Manufacturer: Becton Dickinson and Company

Category: prescription | Type: HUMAN PRESCRIPTION DRUG LABEL
Date: 20220502

ACTIVE INGREDIENTS: DEXTROSE MONOHYDRATE
 100 mg/1 mL

HIGHLIGHTS OF PRESCRIBING INFORMATION

These highlights do not include all the information needed to use 10% DEXTROSE INJECTION safely and effectively. See full prescribing information for DEXTROSE INJECTION.
10% DEXTROSE injection, USP for intravenous use
Initial U.S. Approval: 1940

RECENT MAJOR CHANGES

Dosage and Administration (2.1, 2.2, 2.3) | 9/2021
Contraindications (4) | 9/2021
Warnings and Precautions (5.1, 5.2, 5.3, 5.4, 5.5, 5.6) | 9/2021

1 INDICATIONS AND USAGE

Dextrose Injection is indicated as a source of water and calories. (1)

2 DOSAGE AND ADMINISTRATION

- Only for intravenous infusion. (2.1)
- See full prescribing information for information on preparation, administration, dosing considerations and instructions for use. (2.1, 2.2, 2.3)

3 DOSAGE FORMS AND STRENGTHS

Injection:

- 10% (0.1 grams/mL): 10 grams of dextrose hydrous per 100 mL in flexible containers: 250 mL, 500 mL, and 1000 mL. (3)

4 CONTRAINDICATIONS

- Clinically significant hyperglycemia. (4)
- Known hypersensitivity to dextrose. (4)

5 WARNINGS AND PRECAUTIONS

- Hyperglycemia or Hyperosmolar Hyperglycemic State: Monitor blood glucose and administer insulin as needed. (5.1)
- Hypersensitivity Reactions: Monitor for signs and symptoms and discontinue infusion if reactions occur. (5.2)
- Vein Damage and Thrombosis: Consider central vein when administering more than 5% dextrose or with an osmolarity of at least 900 mOsm/L or when there is peripheral vein irritation, phlebitis, and/or associated pain. (2.2, 5.3)
- Hyponatremia: Avoid in patients with or at risk for hyponatremia. If use cannot be avoided, monitor serum sodium concentrations. (5.4)
- Electrolyte Imbalance and Fluid Overload: Avoid in patients with or at risk for fluid and/or solute overloading. If use cannot be avoided, monitor daily fluid balance, electrolyte concentrations, and acid-base balance, as needed and especially during prolonged use. (5.5)
- Refeeding Syndrome: Monitor severely undernourished patients and slowly increase nutrient intake. (5.6)

6 ADVERSE REACTIONS

The most common adverse reactions are, hyperglycemia, hypersensitivity reactions, hyponatremia, infection both systemic and at the injection site, vein thrombosis or phlebitis, and electrolyte imbalance. (6)

To report SUSPECTED ADVERSE REACTIONS, contact Fresenius Kabi USA, LLC at 1-800-551-7176 or FDA at 1-800-FDA-1088 or www.fda.gov/medwatch.

7 DRUG INTERACTIONS

Other Products that Affect Glycemic Control, Vasopressin or Fluid and/or Electrolyte Balance: Monitor blood glucose concentrations, fluid balance, serum electrolyte concentrations and acid-base balance. (7.1)

8 USE IN SPECIFIC POPULATIONS

Pediatric Use: Increased risk of hypoglycemia/hyperglycemia; monitor serum glucose concentrations. (8.4)

FULL PRESCRIBING INFORMATION

1 INDICATIONS AND USAGE

10% Dextrose Injection is indicated as source of water and calories.

2 DOSAGE AND ADMINISTRATION

2.1 Important Administration Instructions

- 10% Dextrose Injection is intended for intravenous use.
- Peripheral administration of 5% dextrose is generally acceptable, however, consider central vein when administering more than 5% dextrose or with an osmolarity of at least 900 mOsm/L or when there is peripheral vein irritation, phlebitis, and/or associated pain [see Warnings and Precautions (5.3)].
- Do not administer 10% Dextrose Injection simultaneously with blood products through the same administration set because of the possibility of pseudoagglutination or hemolysis.
- To prevent air embolism, use a non-vented infusion set or close the vent on a vented set, avoid multiple connections, do not connect flexible containers in series, fully evacuate residual gas in the container prior to administration, do not pressurize the flexible container to increase flow rates, and if administration is controlled by a pumping device, turn off pump before the container runs dry.
- Prior to infusion, visually inspect the diluted dextrose solution for particulate matter. The solution should be clear and there should be no precipitates. Do not administer unless solution is clear and container is undamaged.
- Use of a final filter is recommended during administration of parenteral solutions, where possible.

2.2 Recommended Dosage

The choice of dextrose concentration, rate and volume depends on the age, weight, clinical and metabolic conditions of the patient and concomitant therapy. Electrolyte supplementation may be indicated according to the clinical needs of the patient.

The administration rate should be governed, especially for premature infants with low birth weight, during the first few days of therapy, by the patient's tolerance to dextrose.

Increase the infusion rate gradually as indicated by frequent monitoring of blood glucose concentrations [see Warnings and Precautions (5.1), Use in Specific Populations (8.4)].

2.3 Instructions for Use

Check flexible container solution composition, lot number, and expiry date. Prior to administration, visually inspect for particulate matter and discoloration.

The intact port caps provides visual tamper evidence. Do not use if a port cap is prematurely removed. Do not remove solution container from its overwrap until immediately before use. Use sterile equipment and aseptic technique.

To Open

1. Place the solution container on a clean, flat surface. Using the pre-cut corner tabs, peel open the overwrap and remove solution container.
2. Check the solution container for leaks by squeezing firmly. If leaks are found, or if the seal is not intact, discard the solution.
3. Do not use if the solution is cloudy or a precipitate is present.

To Add Medication

1. Identify WHITE Additive Port with arrow pointing toward container.
2. Immediately before injecting additives, break off WHITE Additive Port Cap with the arrow pointing toward container.
3. Hold base of WHITE Additive Port horizontally.
4. Insert needle (18 to 23 gauge) horizontally through the center of WHITE Additive Port's septum and inject additives.
5. Mix container contents thoroughly. For high density medication such as potassium chloride, squeeze ports while ports are upright and mix thoroughly.

Preparation for Administration

1. Immediately before inserting the infusion set, break off BLUE Infusion Port Cap with the arrow pointing away from container.
2. Use a non-vented infusion set or close the air-inlet on a vented set.
3. Close the roller clamp of the infusion set.
4. Hold the base of BLUE Infusion Port.
5. Insert spike through BLUE Infusion Port by rotating wrist slightly until the spike is inserted.
6. Suspend solution container from hanger hole
7. For Single Use Only. Discard unused portion.

NOTE: See full directions accompanying administration set.

WARNING: Do not use flexible container in series connections.

3 DOSAGE FORMS AND STRENGTHS

10% Dextrose Injection, USP is a clear, sterile, non-pyrogenic solution of dextrose in single-dose flexible plastic containers

- 10% (0.1 grams/mL): 10 grams of dextrose hydrous per 100 mL in flexible plastic containers: 250 mL, 500 mL, and 1000 mL

4 CONTRAINDICATIONS

The use of Dextrose Injection is contraindicated in patients with:

- Clinically significant hyperglycemia [see Warnings and Precautions (5.1)].
- Known hypersensitivity to dextrose [see Warnings and Precautions (5.2)].

5 WARNINGS AND PRECAUTIONS

5.1 Hyperglycemia and Hyperosmolar Hyperglycemic State

The use of dextrose infusions in patients with impaired glucose tolerance may worsen hyperglycemia. Administration of dextrose at a rate exceeding the patient's utilization rate may lead to hyperglycemia, coma, and death.

Hyperglycemia is associated with an increase in serum osmolality, resulting in osmotic diuresis, dehydration and electrolyte losses [see Warnings and Precautions (5.5)]. Patients with underlying CNS disease and renal impairment who receive dextrose infusions, may be at greater risk of developing hyperosmolar hyperglycemic state.

Monitor blood glucose levels and treat hyperglycemia to maintain levels within normal limits while administering 10% Dextrose Injection. Insulin may be administered or adjusted to maintain optimal blood glucose levels during 10% Dextrose Injection administration.

5.2 Hypersensitivity Reactions

Hypersensitivity and infusion reactions, including anaphylaxis, have been reported with 10% Dextrose Injection [see Adverse Reactions (6)]. Stop infusion immediately and treat patient accordingly if signs or symptoms of a hypersensitivity reaction develop. Appropriate therapeutic countermeasures must be instituted as clinically indicated.

5.3 Vein Damage and Thrombosis

Peripheral administration of 5% Dextrose Injection is generally acceptable, however, consider central vein when administering more than 5% dextrose or with an osmolarity of ≥ at least 900 mOsm/L or when there is peripheral vein irritation, phlebitis, and/or associated pain [see Dosage and Administration (2.1)]. The infusion of hypertonic solutions into a peripheral vein may result in vein irritation, vein damage, and/or thrombosis. The primary complication of peripheral access is venous thrombophlebitis, which manifests as pain, erythema, tenderness or a palpable cord. Remove the catheter as soon as possible, if thrombophlebitis develops.

5.4 Hyponatremia

10% Dextrose Injection is a hypertonic solution [see Description, Table 1 (11)]. In the body, however, glucose containing fluids can become extremely physiologically hypotonic due to rapid glucose metabolization. Monitoring of serum sodium is particularly important for hypotonic fluids.

Depending on the tonicity of the solution, the volume and rate of infusion, and depending on a patient's underlying clinical condition and capability to metabolize glucose, intravenous administration of glucose can cause electrolyte disturbances, most importantly hypo- or hyperosmotic hyponatremia. Monitor serum sodium to minimize the risk of hyponatremia.

The risk for hyponatremia is increased in pediatric patients, elderly patients, postoperative patients, those with psychogenic polydipsia, and in patients treated with medications that increase the risk of hyponatremia (such as diuretics, certain antiepileptic and psychotropic medications). Close clinical monitoring may be warranted.

Acute hyponatremia can lead to acute hyponatremic encephalopathy characterized by headache, nausea, seizures, lethargy and vomiting. Patients with brain edema are at particular risk of severe, irreversible and life-threatening brain injury. Patients at increased risk for developing complications of hyponatremia, such as hyponatremic encephalopathy include pediatric patients; women, in particular, premenopausal women; patients with hypoxemia; and in patients with underlying central nervous system disease [see Use in Specific Populations (8.4, 8.5)].

Avoid Dextrose Injection in patients with or at risk for hyponatremia. If use cannot be avoided, monitor serum sodium concentrations.

Rapid correction of hyponatremia is potentially dangerous with risk of serious neurologic complications. Brain adaptations reducing risk of cerebral edema make the brain vulnerable to injury when chronic hyponatremia is too rapidly corrected, which is known as osmotic demyelination syndrome (ODS). To avoid complications, monitor serum sodium and chloride concentrations, fluid status, acid-base balance, and signs of neurologic complications.

High volume infusion must be used with close monitoring in patients with cardiac or pulmonary failure, and in patients with non-osmotic vasopressin release (including SIADH), due to the risk of hospital-acquired hyponatremia.

5.5 Electrolyte Imbalance and Fluid Overload

Electrolyte deficits, particularly in serum potassium and phosphate, may occur during prolonged use of concentrated dextrose solutions.

Depending on the volume and rate of infusion, the patient's underlying clinical condition and capability to metabolize dextrose, intravenous administration of 10% Dextrose Injection can cause fluid and/or solute overloading resulting in dilution of serum electrolyte concentrations, (including hypoosmotic hyponatremia), overhydration, congested states or pulmonary edema. The risk of dilutional states is inversely proportional to the electrolyte concentrations in the administered solution. The risk of solute overload causing congested states with peripheral and pulmonary edema is directly proportional to the electrolyte concentrations in the solution.

Avoid Dextrose Injection in patients with or at risk for fluid and/or solute overloading. If use cannot be avoided, monitor fluid balance, blood electrolyte levels, concentration of glucose, acid-base balance, correct fluid and electrolyte imbalances during prolonged parenteral therapy or whenever the condition of the patient or the rate of administration warrants such evaluation and acid-base balance as needed and especially during prolonged use. Additional monitoring is recommended for patients with water and electrolyte disturbances that could be aggravated by increased glucose, insulin administration and/or free water load. Patients at increased risk for developing hyponatremic encephalopathy include pediatric patients; elderly patients, women, in particular premenopausal women; patients with hypoxemia; and patients with underlying CNS disease [see Use in Specific Populations (8.4, 8.5)].

5.6 Refeeding Syndrome

Refeeding severely undernourished patients may result in refeeding syndrome, characterized by the intracellular shift of potassium, phosphorus, and magnesium as the patient becomes anabolic. Thiamine deficiency and fluid retention may also develop. To prevent these complications, monitor severely undernourished patients and slowly increase nutrient intake.

6 ADVERSE REACTIONS

The following adverse reactions associated with the use of dextrose injection were identified in clinical trials or postmarketing reports. Because these reactions were reported voluntarily from a population of uncertain size, it is not always possible to estimate their frequency, reliably, or to establish a causal relationship to drug exposure.

The following clinically significant adverse reactions are described elsewhere in the labeling:

- Hyperglycemia and hyperosmolar hyperglycemic state [see Warnings and Precautions (5.1)]
- Hypersensitivity Reactions: anaphylaxis, pruritus, bronchospasm, cyanosis, angioedema, hypotension, pyrexia, chills, and rash [see Warnings and Precautions (5.2)]
- Infusion Site Reactions: infusion site phlebitis, infusion site erythema, vein damage and thrombosis, and infusion site thrombophlebitis [see Warnings and Precautions (5.3)]
- Hyponatremia and hyponatremic encephalopathy [see Warnings and Precautions (5.4)]
- Electrolyte imbalance, fluid overload and hypervolemia [see Warnings and Precautions (5.5)]
- Refeeding syndrome [see Warnings and Precautions (5.6)]
- Pulmonary vascular precipitates

7 DRUG INTERACTIONS

7.1 Other Products that Affect Glycemic Control, Vasopressin or Fluid and/or Electrolyte Balance

Dextrose Injection can affect glycemic control, vasopressin and fluid and/or electrolyte balance [see Warnings and Precautions (5.1, 5.4, 5.5)]. Monitor blood glucose concentrations, fluid balance, serum electrolyte concentrations and acid-base balance when using Dextrose Injection in patients treated with other substances that affect glycemic control, vasopressin or fluid and/or electrolyte balance.

8 USE IN SPECIFIC POPULATIONS

8.1 Pregnancy

Risk Summary

Appropriate administration of 10% Dextrose Injection during pregnancy is not expected to cause adverse developmental outcomes, including congenital malformations. Animal reproduction studies have not been conducted with injectable dextrose solutions.

The estimated background risk of major birth defects and miscarriage for the indicated population is unknown. All pregnancies have a background risk of birth defect, loss, or other adverse outcomes. In the U.S. general population, the estimated background risk of major birth defects and miscarriage in clinically recognized pregnancies is 2 to 4% and 15 to 20%, respectively.

8.2 Lactation

Risk Summary

There are no data on the presence of dextrose in human milk, the effects on a breastfed infant, or the effects on milk production. The lack of clinical data during lactation precludes a clear determination of the risk of 10% Dextrose Injection to an infant during lactation; therefore, the developmental and health benefits of breastfeeding should be considered along with the mother's clinical need for 10% Dextrose Injection and any potential adverse effects on the breastfed infant from 10% Dextrose Injection or from the underlying maternal condition.

8.4 Pediatric Use

The safety profile of 10% Dextrose Injection in pediatric patients is similar to adults.

Neonates, especially premature infants with low birth weight, are at increased risk of developing hypo- or hyperglycemia and therefore need close monitoring during treatment with intravenous glucose infusions to ensure adequate glycemic control in order to avoid potential long-term adverse effects.

Closely monitor plasma electrolyte concentrations in pediatric patients who may have impaired ability to regulate fluids and electrolytes. In very low birth weight infants, excessive or rapid administration of 10% Dextrose Injection may result in increased serum osmolality and risk of intracerebral hemorrhage.

Children (including neonates and older children) are at increased risk of developing hyponatremia as well as for developing hyponatremic encephalopathy [see Warnings and Precautions (5.4)].

8.5 Geriatric Use

Clinical studies of 10% Dextrose Injection did not include sufficient numbers of subjects aged 65 and over to determine whether they respond differently from younger subjects. Elderly patients are at increased risk of developing hyponatremia as well as for developing hyponatremic encephalopathy [see Warnings and Precautions (5.4)]. Other reported clinical experience has not identified differences in responses between the elderly and younger patients. In general, dose selection for an elderly patient should be cautious, usually starting at the low end of the dosing range, reflecting the greater frequency of decreased hepatic, renal, or cardiac function, and of concomitant disease or other drug therapy.

Dextrose is known to be substantially excreted by the kidney, and the risk of toxic reactions to this drug may be greater in patients with impaired renal function. Because elderly patients are more likely to have decreased renal function, care should be taken in dose selection, and it may be useful to monitor renal function.

10 OVERDOSAGE

An increased infusion rate of 10% Dextrose Injection or administration of dextrose solutions can cause hyperglycemia, hyperosmolality, and adverse effects on water and electrolyte balance [see Warnings and Precautions (5.1, 5.5)].

Severe hyperglycemia and severe dilutional hyponatremia, and their complications, can be fatal. Discontinue infusion, reduce dose and institute appropriate corrective measures such as administration of exogenous insulin.

Discontinue infusion and institute appropriate corrective measures in the event of overhydration or solute overload during therapy, with particular attention to CNS, respiratory and cardiovascular systems.

If over-exposure occurs, call your Poison Control Center at 1-800-222-1222 for current information on the management of poisoning or overdosage.

11 DESCRIPTION

10% Dextrose Injection, USP is a sterile, non-pyrogenic solution for fluid replenishment and caloric supply in single dose containers for intravenous administration.

The solution contains no bacteriostatic, antimicrobial agent or added buffer and is intended only for use as a single-dose injection. The pH range is 4.0 (3.2 to 6.5)

Table 1. Contents and Characteristics of Dextrose Injection 10%, USP
Strength | Fill Volume | Amount of Dextrose Hydrous per Container | kcal* per Container | Osmolarity (mOsmol per liter)
Dextrose Injection 10%, USP (0.1 grams/mL) | 250 mL | 25 grams | 85 | 505
Dextrose Injection 10%, USP (0.1 grams/mL) | 500 mL | 50 grams | 170 | 505
Dextrose Injection 10%, USP (0.1 grams/mL) | 1000 mL | 100 grams | 340 | 505
*Caloric value calculated on the basis of 3.4 kcal/g of dextrose, hydrous

Dextrose, USP is chemically designated D-glucose, monohydrate (C6H12O6 • H2O), a hexose sugar freely soluble in water. The molecular weight of dextrose (D-glucose) monohydrate is 198.17. It has the following structural formula:

Water for Injection, USP is chemically designated H2O.

Dextrose is derived from corn.

The flexible container is fabricated from a specially formulated non-plasticized, film containing polypropylene and thermoplastic elastomers (freeflex® bag). The amount of water that can permeate from the container into the overwrap is insufficient to affect the solution significantly. Solutions in contact with the flexible container can leach out certain of the container's chemical components in very small amounts within the expiration period. The suitability of the container material has been confirmed by tests in animals according to USP biological tests for plastic containers.

The flexible container is a closed system, and air is prefilled in the container to facilitate drainage. The container does not require entry of external air during administration.

The container has two ports: one is the administration outlet port for attachment of an intravenous administration set and the other port has a medication site for addition of supplemental medication ([see Instructions for Use (2.3)]). The primary function of the overwrap is to protect the container from the physical environment.

12 CLINICAL PHARMACOLOGY

12.1 Mechanism of Action

Dextrose is oxidized to carbon dioxide and water, yielding energy.

16 HOW SUPPLIED/STORAGE AND HANDLING

10% Dextrose Injection, USP is supplied in single dose flexible plastic containers as follows:

Product Number | Unit of Sale | Strength | Each
1727172105 | NDC 17271-721-05 Package of 30 freeflex® bag | 25 grams per 250 mL (100 mg per mL) | NDC 17271-721-05 One 250 mL freeflex® bag
1727172106 | NDC 17271-721-06 Package of 20 freeflex® bag | 50 grams per 500 mL (100 mg per mL) | NDC 17271-721-06 One 500 mL freeflex® bag
1727172107 | NDC 17271-721-07 Package of 10 freeflex® bag | 100 grams per 1,000 mL (100 mg per mL) | NDC 17271-721-07 One 1000 mL freeflex® bag

Exposure of pharmaceutical products to heat should be minimized. Avoid excessive heat.

STORAGE AND HANDLING

STORE AT: 20° to 25°C (68° to 77°F) [see USP Controlled Room Temperature]; brief exposure up to 40°C/104°F does not adversely affect the product. Keep from freezing.

The container closure is not made with natural rubber latex. Non-PVC, Non-DEHP, Sterile.

17 PATIENT COUNSELING INFORMATION

Inform patients, caregivers, or home healthcare providers of the following risks of 10% Dextrose Injection:

- Hyperglycemia and hyperosmolar hyperglycemic state [see Warnings and Precautions (5.1)]
- Hypersensitivity reactions [see Warnings and Precautions (5.2)]
- Vein damage and thrombosis [see Warnings and Precautions (5.3)]
- Hyponatremia [see Warnings and Precautions (5.4)]
- Electrolyte imbalance and fluid overload [see Warnings and Precautions (5.5)]
- Refeeding syndrome [see Warnings and Precautions (5.6)]

Manufactured for:

Becton, Dickinson and Company
1 Becton Drive
Franklin Lakes, NJ 07417 USA
For product inquiry: 1-800-523-0502
Distributed by BD. Manufactured by Fresenius Kabi.

Made in Germany

451636A

PACKAGE LABEL - PRINCIPAL DISPLAY – 10% Dextrose Bag Label
NDC 17271-721-05
free flex® 250 mL

10% Dextrose Injection, USP

25 grams per 250 mL (100 mg per mL)

For intravenous use. Rx only

PACKAGE LABEL - PRINCIPAL DISPLAY – 10% Dextrose Case Label
NDC 17271-721-05
10% Dextrose Injection, USP

250 mL x 30

PACKAGE LABEL

PACKAGE LABEL - PRINCIPAL DISPLAY PANEL - 10% Dextrose Bag Label

NDC 17271-721-06

free flex® 500 mL

10% Dextrose Injection, USP

50 grams per 500 mL (100 mg per mL)

For intravenous use. Rx only

PACKAGE LABEL

PACKAGE LABEL - PRINCIPAL DISPLAY PANEL - 10% Dextrose Case Label

NDC 17271-721-06

10% Dextrose Injection, USP

500 mL x 20

PACKAGE LABEL

PACKAGE LABEL - PRINCIPAL DISPLAY PANEL - 10% Dextrose Bag Label

NDC 17271-721-07

free flex® 1,000 mL

10% Dextrose Injection, USP

100 grams per 1,000 mL (100 mg per mL)

For intravenous use. Rx only

PACKAGE LABEL

PACKAGE LABEL - PRINCIPAL DISPLAY PANEL - 10% Dextrose Case Label

NDC 17271-721-07

10% Dextrose Injection, USP

1,000 mL x 10